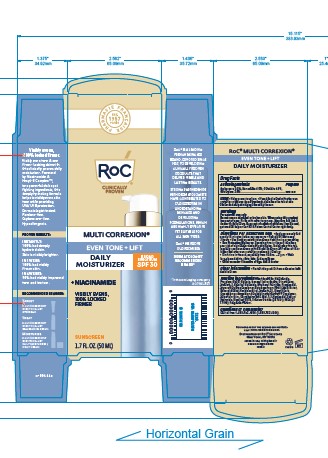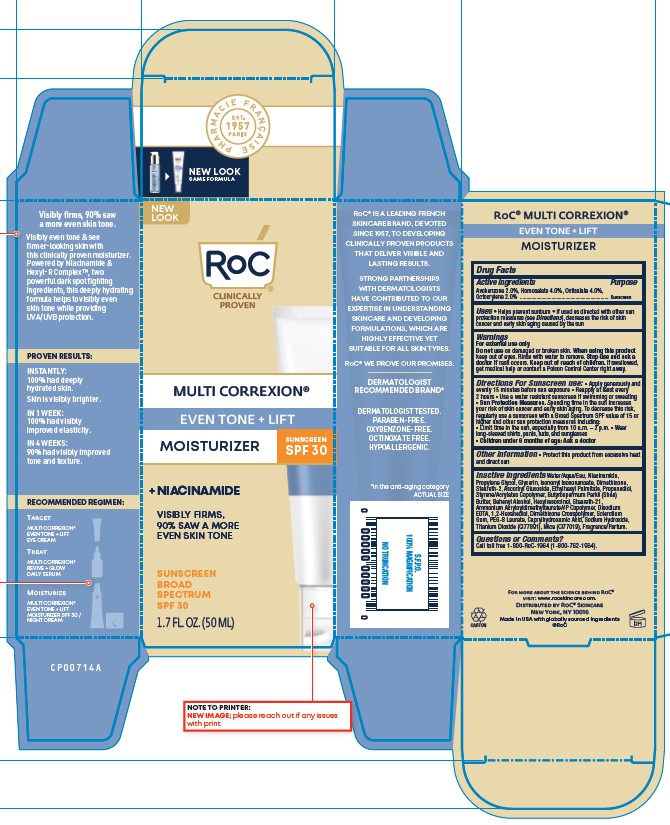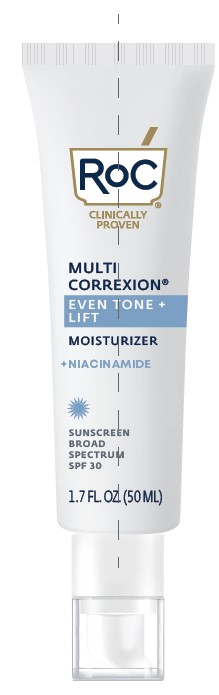 DRUG LABEL: ROC MULTI CORREXION EVEN TONE LIFT DAILY MOISTURIZER SPF30
NDC: 73496-007 | Form: LOTION
Manufacturer: Roc Skincare
Category: otc | Type: HUMAN OTC DRUG LABEL
Date: 20251210

ACTIVE INGREDIENTS: AVOBENZONE 2 mg/100 mL; OCTOCRYLENE 2 mg/100 mL; OCTISALATE 4 mg/100 mL; HOMOSALATE 4 mg/100 mL
INACTIVE INGREDIENTS: AMMONIUM ACRYLOYLDIMETHYLTAURATE/VP COPOLYMER; SODIUM HYDROXIDE; STEARETH-2; ASCORBYL GLUCOSIDE; DOCOSANOL; GLYCERIN; PROPYLENE GLYCOL; STEARETH-21; PROPANEDIOL; WATER; DIMETHICONE; SHEA BUTTER; EDETATE DISODIUM; TITANIUM DIOXIDE; MICA; ISONONYL ISONONANOATE; BETASIZOFIRAN; PEG-8 LAURATE; CAPRYLHYDROXAMIC ACID; 1,2-HEXANEDIOL; HEXYLRESORCINOL; ETHYLHEXYL PALMITATE; NIACINAMIDE

ROC MULTI CORREXION EVEN TONE + LIFT DAILY MOISTURIZER SPF30

ACTIVE INGREDIENT

Avobenzone 2.0%, Homosalate 4.0%, Octisalate 4.0%, Octocrylene 2.0%

Purpose

Sunscreen

Uses

- Helps prevent sunburn
- If used as directed with other sun protection measures (see Directions), decreases the risk of skin cancer and early skin aging caused by the sun

Warnings

- For external use only
- Do not use on damaged or broken skin. When using this product keep out of eyes. Rinse with water to remove. Stop use and ask a doctor if rash occurs. Keep out of reach of children. If swallowed, get medical help or contact Poison Control Center right away

Keep out of reach of children.

Directions for Sunscreen use

- Apply generously and evenly 15 minutes before sun exposure
- Reapply at least every 2 hours
- Use a water resistant sunscreen if swimming or sweating
- Sun Protection Measures. Spending time in the sun increases your risk of skin cancer and early skin aging. To decrease this risk, regularly use a sunscreen with a Broad Spectrum SPF 15 or higher and other sun protection measures including:
- Limit time in the sun, especially from 10 a.m. - 2 p.m.
- Wear long-sleeved shirts, pants, hats, and sunglasses
- Children under 6 months of age: Ask a doctor

Other information

Protect this product from excessive heat and direct sun

INACTIVE INGREDIENT

Water/Aqua/Eau, Niacinamide, Propylene Glycol, Glycerin, Isononyl Isononanoate, Dimethicone, Steareth-2, Ascorbyl Glucoside, Ethylhexyl Palmitate, Propanediol, Styrene/Acrylates Copolymer, Butyrospermum Parkii (Shea) Butter, Behenyl Alcohol, Hexylresorcinol, Steareth-21, Dimethicone Crosspolymer, Ammonium Acryloyldimethyltaurate/VP Copolymer, Sclerotium Gum, Caprylhydroxamic Acid, 1,2-Hexanediol, Sodium Hydroxide, Disodium EDTA, Titanium Dioxide (CI77891), Mica (CI 77019), Fragrance/Parfum.

Questions or Comments?

Call toll free 1-800-RoC-1964 (1-800-762-1964) or 215-273-8755 (collect).